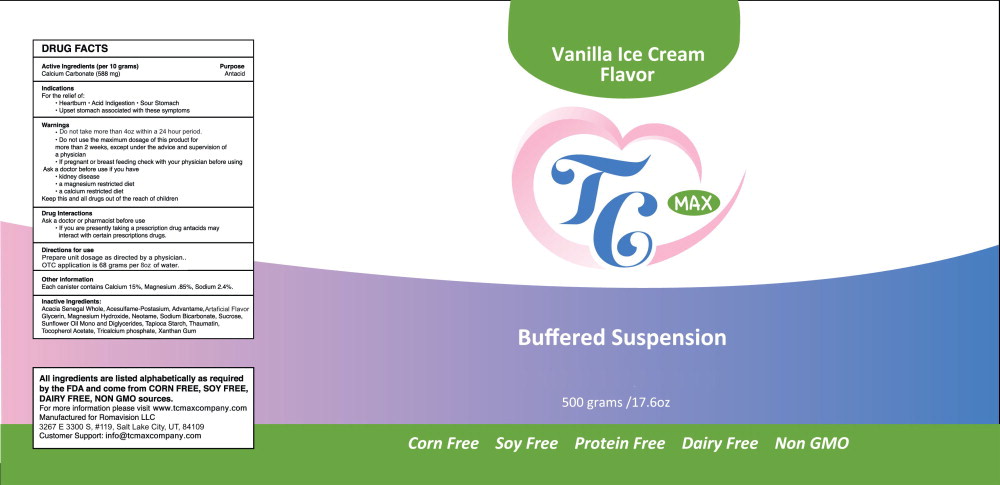 DRUG LABEL: TC Max
NDC: 80733-006 | Form: POWDER, FOR SOLUTION
Manufacturer: Romavision Investing LLC
Category: otc | Type: HUMAN OTC DRUG LABEL
Date: 20231103

ACTIVE INGREDIENTS: calcium carbonate 4 g/237 mL
INACTIVE INGREDIENTS: GLYCERIN; .ALPHA.-TOCOPHEROL ACETATE, DL-; STARCH, TAPIOCA; MALTODEXTRIN; TRICALCIUM PHOSPHATE; SUNFLOWER OIL MONO/DIGLYCERIDES; SUNFLOWER OIL; XANTHAN GUM; NEOTAME; SODIUM BICARBONATE; MAGNESIUM HYDROXIDE; ACESULFAME POTASSIUM; THAUMATIN; SUCROSE; ADVANTAME; ACACIA SENEGAL WHOLE

DRUG FACTS

Active Ingredients (per 10 grams)

Calcium Carbonate (588 mg)

Purpose

Antacid

Indications

For the relief of:

- Heartburn
- Acid Indigestion
- Sour Stomach
- Upset stomach associated with these symptoms

Warnings

- Do not take more than 4 oz within a 24 hour period

- Do not use the maximum dosage of this product for more than 2 weeks, except under the advice and supervision of a physician

PREGNANCY OR BREAST FEEDING

- If pregnant or breast feeding check with your physician before using

Ask a doctor before use if you have

- kidney disease
- a magnesium restricted diet
- a calcium restricted diet

KEEP OUT OF REACH OF CHILDREN

Keep this and all drugs out of the reach of children

Drug Interactions

Ask a doctor or pharmacist before use

- If you are presently taking a prescription drug antacids may interact with certain prescriptions drugs.

Directions for use

Prepare unit dosage as directed by a physician.

OTC application is 68 grams per 8oz of water.

Other information

Each canister contains Calcium 15%, Magnesium .85%, Sodium 2.4%

Inactive Ingredients:

Acacia Senegal Whole, Acesulfame-Postasium, Advantame, Artificial Flavor, Glycerin, Magnesium Hydroxide, Neotame, Sodium Bicarbonate, Sucrose, Sunflower Oil Mono and Diglycerides, Tapioca Starch, Thaumatin, Tocopherol Acetate, Tricalcium phosphate, Xanthan Gum

Principal Display Panel - 500 gram Canister Label

Vanilla Ice Cream
Flavor

TC MAX

Buffered Suspension

500 grams /17.6oz

Corn Free Soy Free Protein Free Dairy Free Non GMO